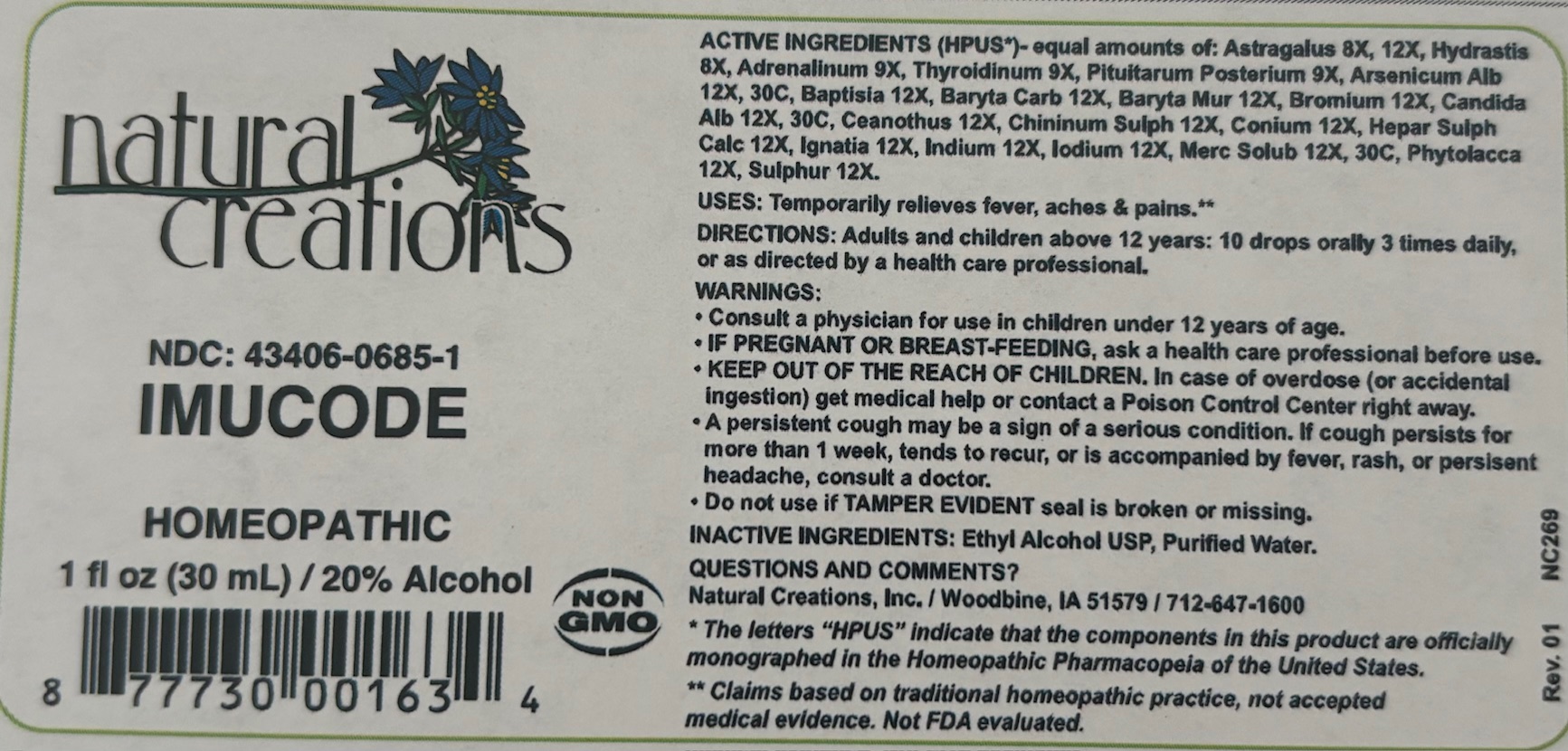 DRUG LABEL: Imucode
NDC: 43406-0685 | Form: LIQUID
Manufacturer: Natural Creations, Inc
Category: homeopathic | Type: HUMAN OTC DRUG LABEL
Date: 20181221

ACTIVE INGREDIENTS: GOLDENSEAL 8 [hp_X]/1 mL; EPINEPHRINE 9 [hp_X]/1 mL; THYROID 9 [hp_X]/1 mL; SUS SCROFA PITUITARY GLAND, POSTERIOR 9 [hp_X]/1 mL; ASTRAGALUS NUTTALLII LEAF 12 [hp_X]/1 mL; BAPTISIA TINCTORIA WHOLE 12 [hp_X]/1 mL; BARIUM CARBONATE 12 [hp_X]/1 mL; BARIUM CHLORIDE DIHYDRATE 12 [hp_X]/1 mL; BROMINE 12 [hp_X]/1 mL; CEANOTHUS AMERICANUS LEAF 12 [hp_X]/1 mL; QUININE SULFATE 12 [hp_X]/1 mL; CONIUM MACULATUM FLOWERING TOP 12 [hp_X]/1 mL; CALCIUM SULFIDE 12 [hp_X]/1 mL; STRYCHNOS IGNATII SEED 12 [hp_X]/1 mL; INDIUM 12 [hp_X]/1 mL; IODINE 12 [hp_X]/1 mL; PHYTOLACCA AMERICANA ROOT 12 [hp_X]/1 mL; SULFUR 12 [hp_X]/1 mL; ARSENIC TRIOXIDE 30 [hp_C]/1 mL; CANDIDA ALBICANS 30 [hp_C]/1 mL; MERCURIUS SOLUBILIS 30 [hp_C]/1 mL
INACTIVE INGREDIENTS: ALCOHOL; WATER

Imucode

ACTIVE INGREDIENT

ACTIVE INGREDIENTS (*HPUS) - equal amounts of: Astragalus 8X, 12X, Hydrastis 8X, Adrenalinum 9X, Thyroidinum 9X, Pituitarum Posterium 9X, Arsenicum Alb 12X, 30C, Baptisia 12X, Baryta Carb 12X, Baryta Mur 12X, Bromium 12X, Candida Alb 12X, 30C, Ceanothus 12X, Chininum Sulph 12X, Conium 12X, Hepar Sulph Calc 12X, Ignatia 12X, Indium 12X, Iodium 12X, Merc Solub 12X, 30C, Phytolacca 12X, Sulphur 12X

INDICATIONS AND USAGE

USES: Temporarily relieves fever, aches & pains.**

PURPOSE

USES: Temporarily relieves fever, aches & pains.**

DOSAGE AND ADMINISTRATION

DIRECTIONS: Adults & children above 12 years: 10 drops orally 3 times daily, or as directed by a health care professional.

KEEP OUT OF REACH OF CHILDREN

KEEP OUT OF THE REACH OF CHILDREN. In case of overdose (or accidental ingestion) get medical help or contact a Poison Control Center right away.

WARNINGS:

- Consult a physician for use in children under 12 years of age.
- IF PREGNANT OR BREAST-FEEDING, ask a health care professional before use.
- KEEP OUT OF THE REACH OF CHILDREN. In case of overdose (or accidental ingestion) get medical help or contact a Poison Control Center right away.
- A persistent cough may be a sign of a serious condition. If cough persists for more than 1 week, tends to recur, or is accompanied by fever, rash, or persistent headache, consult a doctor.
- Do not use if TAMPER EVIDENT seal is broken or missing.

INACTIVE INGREDIENTS: Ethyl Alcohol USP, Purified Water

QUESTIONS & COMMENTS?

Natural Creations, Inc. / Woodbine, IA 51579 / 712-647-1600

REFERENCES

*The letters "HPUS" indicate the components in the product are officially monographed in the Homeopathic Pharmacopeia of the United States.

**Claims based on traditional homeopathic practice, not accepted medical evidence. Not FDA evaluated.

PACKAGE LABEL

NDC:43406-0685-1

Imucode

HOMEOPATHIC

1 fl oz (30mL) / 20% Alcohol